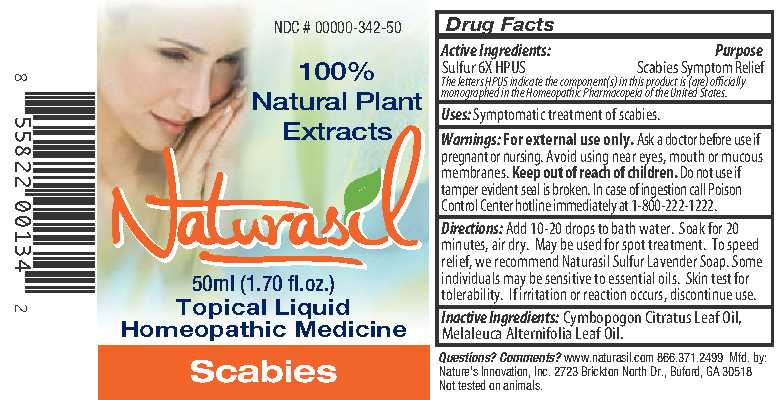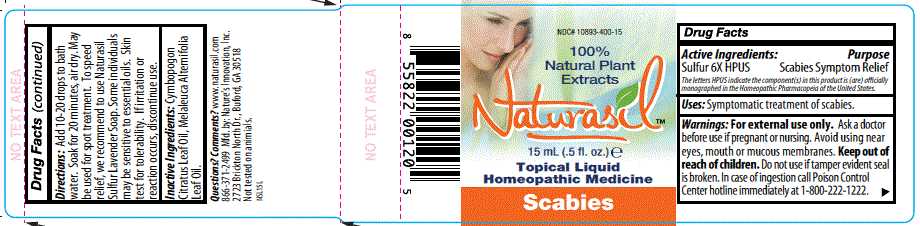 DRUG LABEL: Naturasil
NDC: 10893-400 | Form: LIQUID
Manufacturer: Nature's Innovation, Inc.
Category: homeopathic | Type: HUMAN OTC DRUG LABEL
Date: 20210114

ACTIVE INGREDIENTS: SULFUR 6 [hp_X]/1 1
INACTIVE INGREDIENTS: WEST INDIAN LEMONGRASS OIL; TEA TREE OIL

Scabies Topical Liquid Label

Drug Facts
Active Ingredients:
Sulfur 6X HPUS

DESCRIPTION

The letters HPUS indicate the component(s) in this product is (are) officially monographed in the Homeopathic Pharmacopeia of the United States.

Purpose

Scabies Symptom Relief

INDICATIONS AND USAGE

Uses: Symptomatic treatment scabies.

Warnings: For external use only.

Ask a doctor before use if pregnant or nursing.

OTHER SAFETY INFORMATION

Avoid using near eyes, mouth or mucous membranes.

Keep out of reach of children.

Do not use if tamper evident seal is broken.

OTHER SAFETY INFORMATION

In case of ingestion call Poison Control Center hotline immediately at 1-800-222-1222.

DOSAGE AND ADMINISTRATION

Directions: Add 10-20 drops to bath water. Soak for 20 minutes, air dry. May be used for spot treatment. To speed relief, we recommend to use Naturasil Sulfur Lavender Soap. Some individuals may be sensitive to essential oils. Skin test for tolerability. If irritation or reaction occurs, discontinue use.

Inactive Ingredients:

Cymbopogon Citratus Leaf Oil,

Melaleuca Alternifolia Leaf Oil.

Questions? Comments?

www.naturasil.com 1-866-371-2499

Mfd. by: Nature's Innovation, Inc.,

2723 Brickton North Dr., Buford, GA 30518

Not tested on animals.

PACKAGE LABEL

100% Natural Plant Extracts
Naturasil
ml (fl. oz.)
Topical Liquid
Homeopathic Medicine
Scabies